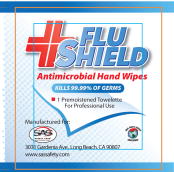 DRUG LABEL: antimicrobial hand wipe
NDC: 65460-3111 | Form: CLOTH
Manufacturer: SAS Safety 
Category: otc | Type: HUMAN OTC DRUG LABEL
Date: 20091118

ACTIVE INGREDIENTS: Alcohol .60 g/1 1
INACTIVE INGREDIENTS: Aloe; water

FLU SHIELD ANTIMICROBIAL HAND WIPES

Active ingredient

Ethyl Alcohol 66.5%

Purpose

Antiseptic

Uses

- for handwashing to decrease bacteria on skin when soap and water is not available

Warnings

For external use only

Flammable: keep away form fire or flame

Do not use in the eyes. If this happens, rinse thoroughly with water.

Stop use and ask a doctor if irritation or redness develop and persist for more than 72 hours

Keep out of reach of children If swallowed get medical help or contact a Poison Control Center right away

Directions

- tear open packet, remove towelette
- wipe hand/wrist areas for 15 seconds and discard
- supervise children under 6 years of age

INACTIVE INGREDIENT

Inactive ingredients aloe vera, fragrance, purified water, triethanolamine

PACKAGE LABEL - PRINCIPAL DISPLAY PANEL – POUCH

FLU SHIELD ANTIMICROBIAL HAND WIPES

Kills 99.99% of germs

1 premoistened towelette

For Professional Use